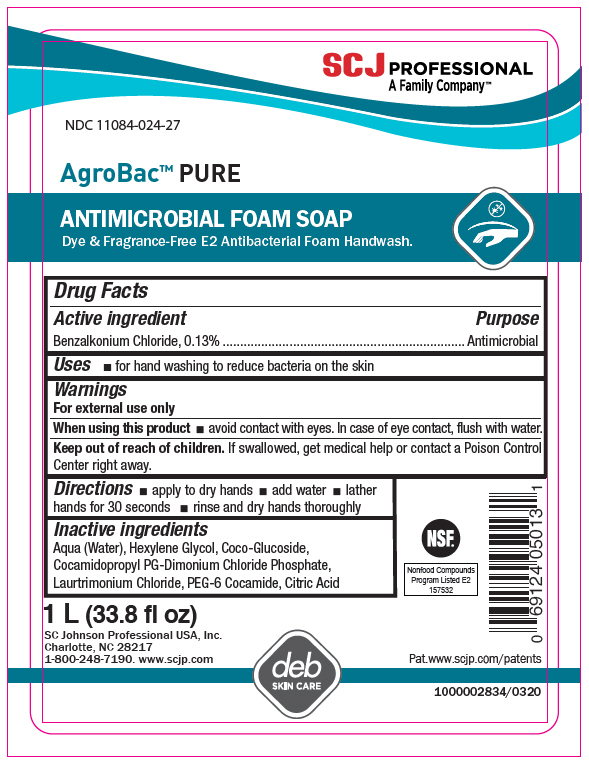 DRUG LABEL: AgroBac Pure FOAM
NDC: 11084-024 | Form: SOLUTION
Manufacturer: SC Johnson Professional USA, Inc.
Category: otc | Type: HUMAN OTC DRUG LABEL
Date: 20241220

ACTIVE INGREDIENTS: BENZALKONIUM CHLORIDE .13 g/100 mL
INACTIVE INGREDIENTS: WATER; HEXYLENE GLYCOL; COCO-GLUCOSIDE; COCAMIDOPROPYL PROPYLENE GLYCOL-DIMONIUM CHLORIDE PHOSPHATE; LAURTRIMONIUM CHLORIDE; PEG-6 COCAMIDE; ANHYDROUS CITRIC ACID

Drug Facts

Active ingredient

Benzalkonium Chloride, 0.13%

Purpose

Antibacterial

Uses

for hand washing to reduce bacteria on the skin

Warnings

For external use only

When using this product

avoid contact with eyes. In case of eye contact, flush with water.

Keep out of reach of children.

If swallowed, get medical help or contact a Poison Control Center right away.

Directions

apply to dry hands

add water

lather hands for 30 seconds

rinse and dry hands thoroughly

Inactive ingredients

Aqua (Water), Hexylene Glycol, Coco-Glucoside, Cocamidopropyl PG-Dimonium Chloride Phosphate, Laurtrimonium Chloride, PEG-6 Cocamide, Citric Acid

PRINCIPAL DISPLAY PANEL - 1 L Bottle Label

SCJ PROFESSIONAL
A Family Company™

NDC 11084-024-27

AgroBac™ PURE

ANTIMICROBIAL FOAM SOAP
Dye & Fragrance-Free E2 Antibacterial Foam Handwash.

NSF®
Nonfood Compounds
Program Listed E2
157532

1 L (33.8 fl oz)

SC Johnson Professional USA, Inc.
Charlotte, NC 28217
1-800-248-7190. www.scjp.com

Pat.www.scjp.com/patents

deb
SKIN CARE

1000002834/0320